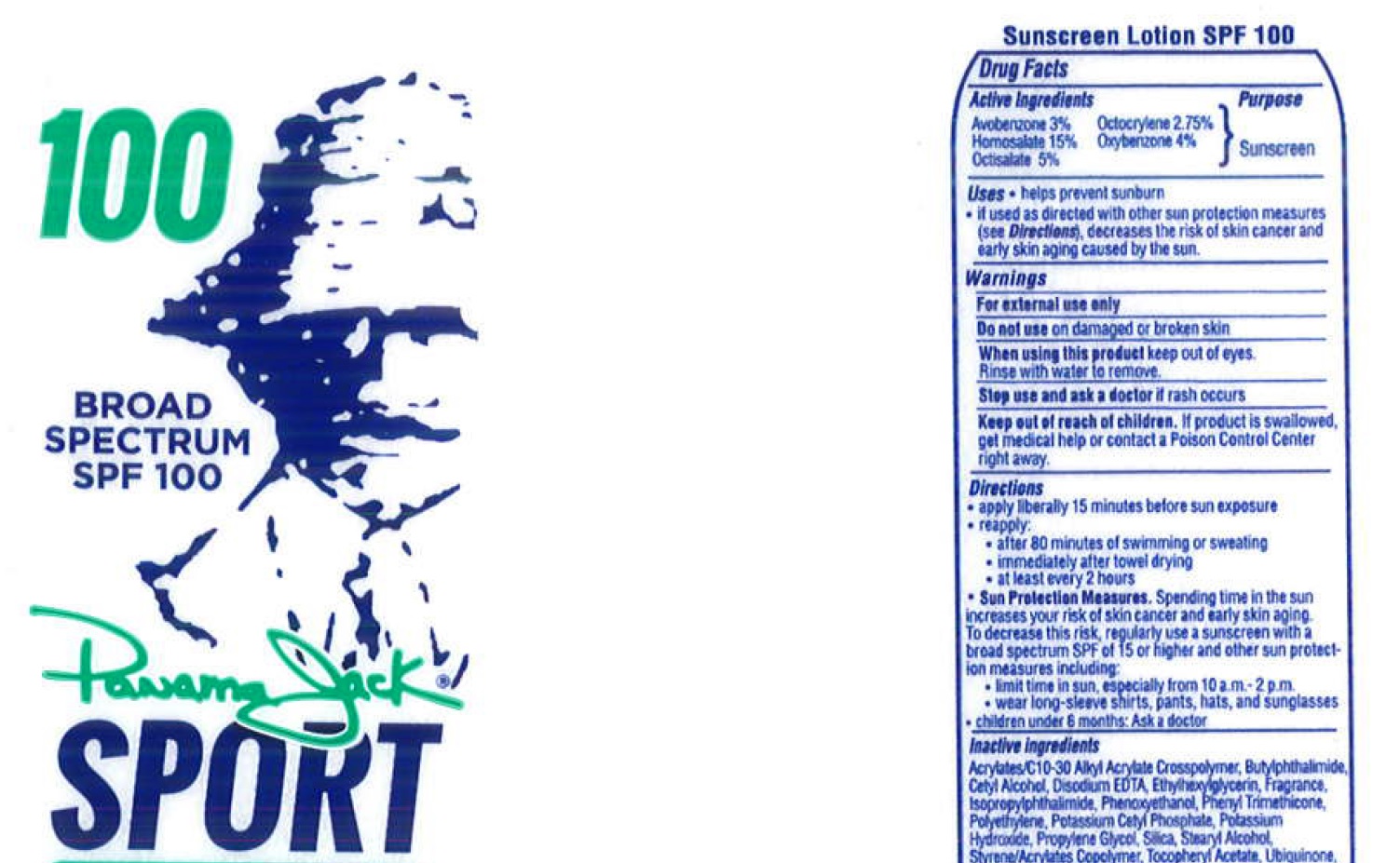 DRUG LABEL: Panama Jack
NDC: 58443-0257 | Form: LOTION
Manufacturer: Prime Enterprises Inc.
Category: otc | Type: HUMAN OTC DRUG LABEL
Date: 20200117

ACTIVE INGREDIENTS: OXYBENZONE 38.04 mg/1 mL; AVOBENZONE 28.58 mg/1 mL; OCTISALATE 47.55 mg/1 mL; OCTOCRYLENE 26.15 mg/1 mL; HOMOSALATE 142.65 mg/1 mL
INACTIVE INGREDIENTS: CETYL ALCOHOL; WATER; SILICON DIOXIDE; STEARYL ALCOHOL; PHENOXYETHANOL; ETHYLHEXYLGLYCERIN; POTASSIUM CETYL PHOSPHATE; PROPYLENE GLYCOL; BUTYL METHACRYLATE/METHYL METHACRYLATE/METHACRYLIC ACID/STYRENE CROSSPOLYMER; .ALPHA.-TOCOPHEROL ACETATE; UBIDECARENONE; POTASSIUM HYDROXIDE; UNDECYLCRYLENE DIMETHICONE (10000 MW); EDETATE DISODIUM; PHENYL TRIMETHICONE; HIGH DENSITY POLYETHYLENE; CARBOMER COPOLYMER TYPE A; CARBOMER INTERPOLYMER TYPE A (ALLYL SUCROSE CROSSLINKED); ISOPROPYLPHTHALIMIDE; N-BUTYLPHTHALIMIDE

100 Broad Spectrum SPF 100 Panama Jack Sport Sunscreen Lotion

Active Ingredients

Avobenzone 3% Octocrylene 2.75%

Homosalate 15% Oxybenzone 4%

Octisalate 5%

Purpose

Sunscreen

Uses

• helps prevent sunburn

• if used as directed with other sun protection measures (see Directions), decreases the risk of skin cancer and early skin aging caused by the sun.

Warnings

For external use only

Do not use on damaged or broken skin

When using this product keep out of eyes.

Rinse with water to remove.

Stop use and ask a doctor if rash occurs

Keep out of reach of children. If product is swallowed, get medical help or contact a Poison Control Center right away.

Directions

• apply liberally 15 minutes before sun exposure

• reapply:

• after 80 minutes of swimming or sweating

• immediately after towel drying

• at least every 2 hours

• Sun Protection Measures. Spending time in the sun increases your risk of skin cancer and early skin aging. To decrease this risk, regularly use a sunscreen with broad spectrum SPF of 15 or higher and other sun protection measures including:

• limit time in the sun, especially from 10 a.m. – 2 p.m.

• wear long-sleeve shirts, pants, hats, and sunglasses

• children under 6 months: Ask a doctor

Inactive ingredients

Acrylates/C10-30 Alkyl Acrylate Crosspolymer, Butylphthalimide, Cetyl Alcohol, Disodium EDTA, Ethylhexylglycerin, Fragrance, Isopropylphthalimide, Phenoxyethanol, Phenyl Trimethicone, Polyethylene, Potassium Cetyl Phosphate, Potassium Hydroxide, Propylene Glycol, Silica, Stearyl Alcohol, Styrene/Acrylates Copolymer, Tocopheryl Acetate, Ubiquinone, Undecylcrylene Dimethicone, Water

Other information

• may stain some fabrics.

• protect this product from excessive heat and direct sun

Questions or comments?

Call toll free 1-800-840-5225